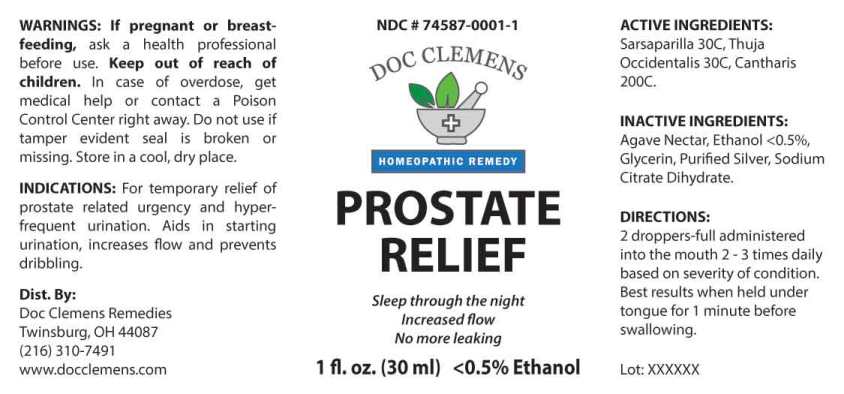 DRUG LABEL: Prostate Relief
NDC: 74587-0001 | Form: LIQUID
Manufacturer: Feel Good Pets LLC
Category: homeopathic | Type: HUMAN OTC DRUG LABEL
Date: 20201002

ACTIVE INGREDIENTS: SMILAX ORNATA ROOT 30 [hp_C]/1 mL; THUJA OCCIDENTALIS LEAFY TWIG 30 [hp_C]/1 mL; LYTTA VESICATORIA 200 [hp_C]/1 mL
INACTIVE INGREDIENTS: GLYCERIN; SILVER; TRISODIUM CITRATE DIHYDRATE; AGAVE TEQUILANA JUICE; ALCOHOL

Drug Facts:

ACTIVE INGREDIENTS:

Sarsaparilla (Smilax Regelii) 30C, Thuja Occidentalis 30C, Cantharis 200C.

INDICATIONS:

For temporary relief of prostate related urgency and hyperfrequent urination. Aids in starting urination, increases flow and prevents dribbling.

WARNINGS:

If pregnant or breast-feeding, ask a health professional before use.

Keep out of reach of children. In case of overdose, get medical help or contact a Poison Control Center right away.

Do not use if tamper evident seal is broken or missing.

Store in a cool, dry place.

Keep out of reach of children. In case of overdose, get medical help or contact a Poison Control Center right away.

DIRECTIONS:

2 droppers-full administered into the mouth 2-3 times daily based on severity of condition. Best results when held unde tongue for 1 minute before swallowing.

INDICATIONS:

For temporary relief of prostate related urgency and hyperfrequent urination. Aids in starting urination, increases flow and prevents dribbling.

INACTIVE INGREDIENTS:

Agave Nectar, Ethanol <0.5%, Glycerin, Purified Silver, Sodium Citrate Dihydrate.

QUESTIONS:

Dist. By:

Doc Clemens Remedies
Twinsburg, OH 44087
(216) 310-7491

www.docclemens.com

PACKAGE LABEL DISPLAY:

NDC 74587-0001-1

DOC CLEMENS

HOMEOPATHIC REMEDY

PROSTATE RELIEF

1 fl. oz. (30 ml)